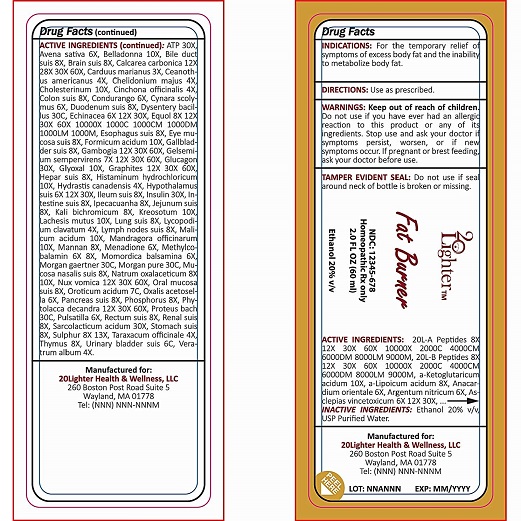 DRUG LABEL: 20 Lighter Fat Burner
NDC: 70418-002 | Form: LIQUID
Manufacturer: 20Lighter Health & Wellness, LLC
Category: homeopathic | Type: HUMAN PRESCRIPTION DRUG LABEL
Date: 20160615

ACTIVE INGREDIENTS: SEMECARPUS ANACARDIUM JUICE 8 [hp_X]/60 mL; .ALPHA.-LIPOIC ACID 6 [hp_X]/60 mL; BELLADONNA LEAF 10 [hp_X]/60 mL; EQUOL, (+)- 8 [hp_X]/60 mL; SUS SCROFA ESOPHAGUS 8 [hp_X]/60 mL; FORMIC ACID 10 [hp_X]/60 mL; SUS SCROFA GALLBLADDER 8 [hp_X]/60 mL; INSULIN ARGINE 30 [hp_X]/60 mL; SULFUR 13 [hp_X]/60 mL; HUMAN THYMUS 8 [hp_X]/60 mL; SUS SCROFA URINARY BLADDER 6 [hp_C]/60 mL; VERATRUM ALBUM ROOT 4 [hp_X]/60 mL; CYNANCHUM VINCETOXICUM ROOT 6 [hp_X]/60 mL; PORK LIVER 8 [hp_X]/60 mL; CARAPICHEA IPECACUANHA WHOLE 8 [hp_X]/60 mL; LYCOPODIUM CLAVATUM WHOLE 4 [hp_X]/60 mL; MENADIONE 6 [hp_X]/60 mL; METHYLCOBALAMIN 8 [hp_X]/60 mL; MOMORDICA BALSAMINA WHOLE 8 [hp_X]/60 mL; STRYCHNOS NUX-VOMICA SEED 60 [hp_X]/60 mL; SUS SCROFA ORAL MUCOSA 8 [hp_X]/60 mL; SUS SCROFA PANCREAS 8 [hp_X]/60 mL; PHOSPHORUS 8 [hp_X]/60 mL; PHYTOLACCA AMERICANA ROOT 60 [hp_X]/60 mL; SUS SCROFA DUODENUM 6 [hp_X]/60 mL; HYDRASTIS CANADENSIS WHOLE 4 [hp_X]/60 mL; GELSEMIUM SEMPERVIRENS ROOT 60 [hp_X]/60 mL; CEANOTHUS AMERICANUS LEAF 4 [hp_X]/60 mL; SUS SCROFA ILEUM 8 [hp_X]/60 mL; LACHESIS MUTA VENOM 10 [hp_X]/60 mL; SUS SCROFA LUNG 10 [hp_X]/60 mL; SUS SCROFA NASAL MUCOSA 8 [hp_X]/60 mL; PULSATILLA VULGARIS 6 [hp_X]/60 mL; LACTIC ACID, L- 30 [hp_X]/60 mL; ADENOSINE TRIPHOSPHATE 30 [hp_X]/60 mL; AVENA SATIVA FLOWERING TOP 6 [hp_X]/60 mL; MILK THISTLE 3 [hp_X]/60 mL; CHELIDONIUM MAJUS 4 [hp_X]/60 mL; CHOLESTEROL 10 [hp_X]/60 mL; GLUCAGON 30 [hp_X]/60 mL; SILVER NITRATE 6 [hp_X]/60 mL; MARSDENIA CUNDURANGO WHOLE 6 [hp_X]/60 mL; CYNARA SCOLYMUS LEAF 6 [hp_X]/60 mL; YEAST MANNAN 10 [hp_X]/60 mL; SUS SCROFA CEREBRUM 8 [hp_X]/60 mL; SHIGELLA DYSENTERIAE 30 [hp_C]/60 mL; ECHINACEA ANGUSTIFOLIA 8 [hp_X]/60 mL; SUS SCROFA EYE 8 [hp_X]/60 mL; SUS SCROFA HYPOTHALAMUS 6 [hp_X]/60 mL; PORK INTESTINE 8 [hp_X]/60 mL; SUS SCROFA JEJUNUM 8 [hp_X]/60 mL; MANDRAGORA OFFICINARUM ROOT 10 [hp_X]/60 mL; PROTEUS INCONSTANS 30 [hp_C]/60 mL; PORK KIDNEY 8 [hp_X]/60 mL; SUS SCROFA STOMACH 8 [hp_X]/60 mL; GAMBOGE 12 [hp_X]/60 mL; OYSTER SHELL CALCIUM CARBONATE, CRUDE 12 [hp_X]/60 mL; TARAXACUM OFFICINALE 4 [hp_X]/60 mL; WOOD CREOSOTE 10 [hp_X]/60 mL; SUS SCROFA BILE DUCT 8 [hp_X]/60 mL; GRAPHITE 60 [hp_X]/60 mL; GLYOXAL 10 [hp_X]/60 mL; CINCHONA OFFICINALIS BARK 4 [hp_X]/60 mL; SUS SCROFA COLON 8 [hp_X]/60 mL; .ALPHA.-KETOGLUTARIC ACID 10 [hp_X]/60 mL
INACTIVE INGREDIENTS: SODIUM DIETHYL OXALACETATE; ALCOHOL; WATER; HISTAMINE DIHYDROCHLORIDE

PURPOSE

For temporary relief of symptms of excess body fat and the inability to metabolize body fat.

WARNING

Do not use if you have ever had an allergic reaction to this product or any of it ingredients.

Stop use and ask your doctor if symptoms persist, worsen, or if new symptoms occur.

If pregnant or breastfeeding, ask your doctor before use.

OTHER SAFETY INFORMATION

TAMPER EVIDENT SEAL: Do not use if seal around neck of bottle is broken or missing.

INDICATIONS AND USAGE

For temporary relief of symptms of excess body fat and the inability to metabolize body fat.

Use as prescribed.

ACTIVE INGREDIENTS

20L - A PEPTIDES

20L-B PEPTIDES

A-KETOGLUTARICUM ACIDUM

ANACARDIUM ORIENTALE
A-LIPOICUM ACIDUM
ARGENTUM NITRICUM
ASCLEPIAS VINCETOXICUM
ATP
AVENA SATIVA
BELLADONNA
BILE DUCT SUIS
BRAIN SUIS
CALCAREA CARBONICA
CARDUUS MARIANUS
CEANOTHUS AMERICANUS
CHELIDONIUM MAJUS
CHOLESTERINUM
CINCHONA OFFICINALIS
COLON SUIS
CONDURANFO
CYNARA SCOLYMUS
DUODENUM SUIS
DYSENTERY BACILLUS
ECHINACEA
EQUOL
ESOPHAGUS SUIS
EYE MUCOSA SUIS
FORMICUM ACIDUM
GALLBLADER SUIS
GAMBOGIA
GELSEMIUM SEMPERVIRENS
GLUCAGON
GLYOXAL
GRAPHITES
HEPAR SUIS
HISTAMINUM HYDROCHLORICUM
HYDRASTIS CANADENSIS
HYPOTHALMUS SUIS
ILEUM SUIS
INSULIN
INTESTINE SUIS
IPECACUANHA
JEJUNUM SUIS
KALI BICHROMICUM
KREOSOTUM
LACHESIS MUTUS
LUNG SUIS
LYCOPODIUM CLAVATUM
LYMPH NODES SUIS
MALICUM ACIDUM
MANDRAGORA OFFICINARUM
MANNAN
MENADIONE
METHYLCOBALAMIN
MOMORDICA BALSAMINA
MORGAN GAERTNER
MORGAN PURE
MUCSA NASALIS SUIS
NATRUM OXALACETICUM
NUX VOMICA
ORAL MUCOSA SUIS
PANCREAS SUIS
PHOSPHORUS
PHYTOLACCA DECANDRA
PROTEUS BACH
PULSATILLA
RECTUM SUIS
RENAL SUI
SARCOLACTICUM ACIDUM
STOMACH SUIS
SULPHUR
TARAXACUM OFFICINALE
THYMUS
URINARY BLADDER SUIS
VERATRUM ALBUM

INACTIVE INGREDIENTS

ETHANOL 20% V/V

USP PURIFIED WATER

DOSAGE AND ADMINISTRATION

Use as prescribed

KEEP OUT OF REACH OF CHILDREN